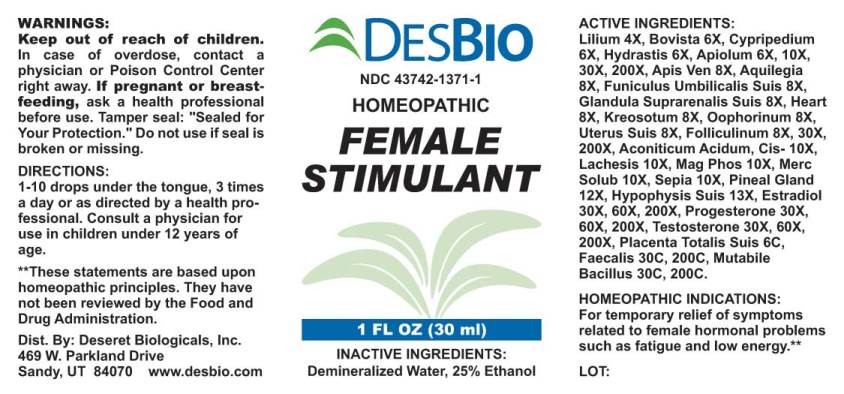 DRUG LABEL: Female Stimulant
NDC: 43742-1371 | Form: LIQUID
Manufacturer: Deseret Biologicals, Inc.
Category: homeopathic | Type: HUMAN OTC DRUG LABEL
Date: 20210122
DEA Schedule: CIII

ACTIVE INGREDIENTS: LILIUM LANCIFOLIUM WHOLE FLOWERING 4 [hp_X]/1 mL; LYCOPERDON UTRIFORME FRUITING BODY 6 [hp_X]/1 mL; CYPRIPEDIUM PARVIFLORUM VAR. PUBESCENS ROOT 6 [hp_X]/1 mL; GOLDENSEAL 6 [hp_X]/1 mL; APIOLE (PARSLEY) 6 [hp_X]/1 mL; APIS MELLIFERA VENOM 8 [hp_X]/1 mL; AQUILEGIA VULGARIS 8 [hp_X]/1 mL; SUS SCROFA UMBILICAL CORD 8 [hp_X]/1 mL; SUS SCROFA ADRENAL GLAND 8 [hp_X]/1 mL; PORK HEART 8 [hp_X]/1 mL; WOOD CREOSOTE 8 [hp_X]/1 mL; SUS SCROFA OVARY 8 [hp_X]/1 mL; SUS SCROFA UTERUS 8 [hp_X]/1 mL; ESTRONE 8 [hp_X]/1 mL; ACONITIC ACID, (Z)- 10 [hp_X]/1 mL; LACHESIS MUTA VENOM 10 [hp_X]/1 mL; MAGNESIUM PHOSPHATE, DIBASIC TRIHYDRATE 10 [hp_X]/1 mL; MERCURIUS SOLUBILIS 10 [hp_X]/1 mL; SEPIA OFFICINALIS JUICE 10 [hp_X]/1 mL; SUS SCROFA PINEAL GLAND 12 [hp_X]/1 mL; SUS SCROFA PITUITARY GLAND 13 [hp_X]/1 mL; ESTRADIOL 30 [hp_X]/1 mL; PROGESTERONE 30 [hp_X]/1 mL; TESTOSTERONE 30 [hp_X]/1 mL; SUS SCROFA PLACENTA 6 [hp_C]/1 mL; ALCALIGENES FAECALIS 30 [hp_C]/1 mL; ESCHERICHIA COLI 30 [hp_C]/1 mL
INACTIVE INGREDIENTS: WATER; ALCOHOL

Drug Facts:

ACTIVE INGREDIENTS:

Lilium Tigrinum 4X, Bovista 6X, Cypripedium Pubescens 6X, Hydrastis Canadensis 6X, Apiolum 6X, 10X, 30X, 200X, Apis Venenum Purum 8X, Aquilegia Vulgaris 8X, Funiculus Umbilicalis Suis 8X, Glandula Suprarenalis Suis 8X, Heart (Suis) 8X, Kreosotum 8X, Oophorinum (Suis) 8X, Uterus (Suis) 8X, Folliculinum 8X, 30X, 200X, Aconiticum Acidum CIS 10X, Lachesis Mutus 10X, Magnesia Phosphorica 10X, Mercurius Solubilis 10X, Sepia 10X, Pineal Gland (Suis) 12X, Hypophysis Suis 13X, Estradiol 30X, 60X, 200X, Progesterone 30X, 60X, 200X, Testosterone 30X, 60X, 200X, Placenta Totalis Suis 6C, Bacillus Faecalis 30C, 200C, Mutabile Bacillus (Bach) 30C, 200C

HOMEOPATHIC INDICATIONS:

For temporary relief of symptoms related to female hormonal problems such as fatigue and low energy.**

**These statements are based upon traditional homeopathic principles. They have not been reviewed by the Food and Drug Administration.

WARNINGS:

Keep out of reach of children. In case of overdose, contact physician or a Poison Control Center right away.

If pregnant or breast-feeding, ask a health professional before use.

Tamper seal: "Sealed for Your Protection." Do not use if seal is broken or missing.

Keep out of reach of children. In case of overdose, contact physician or a Poison Control Center right away.

DIRECTIONS:

1-10 drops under the tongue, 3 times a day or as directed by a health professional. Consult a physician for use in children under 12 years of age.

HOMEOPATHIC INDICATIONS:

For temporary relief of symptoms related to female hormonal problems such as fatigue and low energy.**

**These statements are based upon traditional homeopathic principles. They have not been reviewed by the Food and Drug Administration.

INACTIVE INGREDIENTS:

Demineralized Water, 25% Ethanol

QUESTIONS:

Dist. By: Deseret Biologicals, Inc.
469 W. Parkland Drive
Sandy, UT 84070 www.desbio.com

PACKAGE LABEL DISPLAY:

DESBIO

NDC 43742-1371-1

HOMEOPATHIC

FEMALE

STIMULANT

1 FL OZ (30 ml)